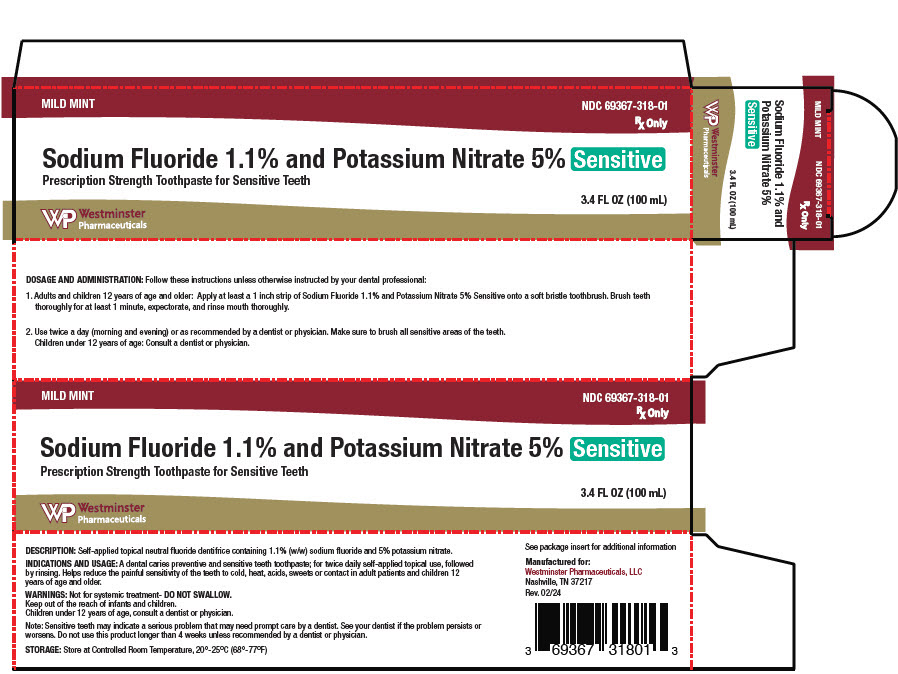 DRUG LABEL: Sodium Fluoride and Potassium Nitrate
NDC: 69367-318 | Form: GEL
Manufacturer: Westminster Pharmaceuticals, LLC
Category: prescription | Type: HUMAN PRESCRIPTION DRUG LABEL
Date: 20240418

ACTIVE INGREDIENTS: SODIUM FLUORIDE 5.8 mg/1 mL; POTASSIUM NITRATE 57.5 mg/1 mL
INACTIVE INGREDIENTS: WATER; SODIUM BENZOATE; SACCHARIN SODIUM; TITANIUM DIOXIDE; DIBASIC CALCIUM PHOSPHATE DIHYDRATE; SORBITOL; FD&C BLUE NO. 1; D&C YELLOW NO. 10; HYDRATED SILICA; GLYCERIN; XANTHAN GUM; SODIUM LAURYL SULFATE

Sodium Fluoride 1.1% and Potassium Nitrate 5% Sensitive

Rx Only

1.1% Sodium fluoride, 5% Potassium Nitrate

Prescription Strength Toothpaste for Sensitive Teeth

DESCRIPTION

Self-topical neutral fluoride toothpaste containing 1.1% (w/w) sodium fluoride and 5% potassium nitrate.

Active Ingredients

Sodium Fluoride 1.1% (w/w)

Potassium Nitrate 5%

Inactive Ingredients

D&C Yellow No.10, Dicalcium Phosphate, FD&C Blue No.1, Glycerin, Hydrated Silica, Mint Flavor, Purified Water, Sodium Benzoate, Sodium Luaryl Sulfate, Sodium Saccharin, Sorbitol, Titanium Dioxide, Xanthum Gum.

CLINICAL PHARMACOLOGY

Frequent topical applications to the teeth with preparations having a relatively high fluoride content increase tooth resistance to acid dissolution and enhance penetration of the fluoride ion into tooth enamel.

INDICATIONS AND USAGE

A dental caries preventive and sensitive teeth toothpaste; for twice daily self-applied topical use, followed by rinsing. Helps reduce the painful sensitivity of the teeth to cold, heat, acid, sweets or contact in adult patients and children 12 years of age and older. It is well established that 1.1% sodium fluoride is safe and extraordinarily effective as a caries preventive when applied frequently with mouthpiece applicators.^1-4 Sodium Fluoride 1.1% and Potassium Nitrate 5% Sensitive in a squeeze-tube is easily applied onto a toothbrush. This prescription toothpaste should be used twice daily in place of your regular toothpaste, unless otherwise instructed by your dental professional. May be used whether or not drinking water is fluoridated, since topical fluoride cannot produce fluorosis. (See WARNINGS for exception.)

CONTRAINDICATIONS

Do not use in pediatric patients under age 12 years unless recommended by a dentist or physician.

WARNINGS

Not for systemic treatment - DO NOT SWALLOW. Keep out of the reach of children. Children under 12 years of age, consult a dentist or physician.

Note: Sensitive teeth may indicate a serious problem that may need prompt care by a dentist. See your dentist if the problem persists or worsens. Do not use this product longer than 4 weeks unless recommended by a dentist or physician.

PRECAUTIONS

General

Not for systemic treatment. DO NOT SWALLOW.

Carcinogenesis, Mutagenesis, Impairment of Fertility

In a study conducted in rodents, no carcinogenesis was found in male and female mice and female rats treated with fluoride at dose levels ranging from 4.1 to 9.1 mg/kg of body weight. Equivocal evidence of carcinogenesis was reported in male rats treated with 2.5 and 4.1 mg/kg of body weight. In a second study, no carcinogenesis was observed in rats, males or females, treated with fluoride up to 11.3 mg/kg of body weight. Epidemiological data provide no credible evidence for an association between fluoride, either naturally occurring or added to drinking water, and risk of human cancer.

Fluoride ion is not mutagenic in standard bacterial systems. It has been shown that fluoride ion has potential to induce chromosome aberrations in cultured human and rodent cells at doses much higher than those to which humans are exposed. In vivo data are conflicting. Some studies report chromosome damage in rodents, while other studies using similar protocols report negative results.

Potential adverse reproductive effects of fluoride exposure in humans has not been adequately evaluated. Adverse effects on reproduction were reported for rats, mice, fox, and cattle exposed to 100 ppm or greater concentrations of fluoride in their diet or drinking water. Other studies conducted in rats demonstrated that lower concentrations of fluoride (5 mg/kg of body weight) did not result in impaired fertility and reproductive capabilities.

Pregnancy

Teratogenic Effects

Pregnancy Category B

It has been shown that fluoride crosses the placenta of rats, but only 0.01% of the amount administered is incorporated in fetal tissue. Animal studies (rats, mice, rabbits) have shown that fluoride is not a teratogen. Maternal exposure to 12.2 mg fluoride/kg of body weight (rats) or 13.1 mg/kg of body weight (rabbits) did not affect the litter size or fetal weight and did not increase the frequency of skeletal or visceral malformations. There are no adequate and well-controlled studies in pregnant women. However, epidemiological studies conducted in areas with high levels of naturally fluoridated water showed no increase in birth defects. Heavy exposure to fluoride during in utero development may result in skeletal fluorosis, which becomes evident in childhood.

Nursing Mothers

It is not known if fluoride is excreted in human milk. However, many drugs are excreted in milk, and caution should be exercised when products containing fluoride are administered to a nursing woman. Reduced milk production was reported in farm-raised fox when the animals were fed a diet containing a high concentration of fluoride (98-137 mg/kg of body weight). No adverse effects on parturition, lactation, or offspring were seen in rats administered fluoride up to 5 mg/kg of body weight.

Pediatric Use

Safety and effectiveness in pediatric patients below the age of 12 years have not been established. Please refer to the CONTRAINDICATIONS and WARNINGS sections.

Geriatric Use

No studies of Sodium Fluoride 1.1% and Potassium Nitrate 5% Sensitive have been conducted to determine whether subjects aged 65 and over respond differently from younger subjects.

ADVERSE REACTIONS

Allergic reactions and other idiosyncrasies have been rarely reported.

To report SUSPECTED ADVERSE REACTIONS, contact Westminster Pharmaceuticals, LLC at 1-844-221-7294 or FDA at 1-800-FDA-1088 or www.fda.gov/medwatch.

OVERDOSAGE

Accidental ingestion of large amounts of fluoride may result in acute burning in the mouth and sore tongue. Nausea, vomitting, and diarrhea may occur soon after ingestion (within 30 minutes) and are accompanied by salivation, hematemesis, and epigastric cramping abdominal pain. These symptoms may persist for 24 hours. If less than 5 mg fluoride/kg body weight (i.e. less than 2.3 mg fluoride/lb body weight) have been ingested, give calcium (e.g.milk) orally to relieve gastrointestinal symptoms and observe for a few hours. If more than 5 mg fluoride/kg body weight (i.e. more than 2.3 mg fluoride/lb body weight) have been ingested, induce vomitting, give orally soluble calcium (e.g. milk, 5% calcium gluconate or calcium lactate solution) and immediately seek medical assistance. For accidental ingestion of more than 15 mg fluoride/kg of body weight (i.e. more than 6.9 mg fluoride/lb body weight), induce vomitting and admit immediately to a hospital facility.

A treatment dose (a thin ribbon) of Sodium Fluoride 1.1% and Potassium Nitrate 5% Sensitive contains approximately 2.5 mg fluoride. A 3.4 FL OZ (100 mL) tube contains approximately 575 mg fluoride.

DOSAGE AND ADMINISTRATION

Follow these instructions unless otherwise instructed by your dental professional:

1. Adults and children 12 years of age or older, apply at least a 1 inch strip of Sodium Fluoride 1.1% and Potassium Nitrate 5% Sensitive onto a soft bristle toothbrush. Brush teeth thoroughly for at least 1 minute, expectorate, and rinse mouth thoroughly.
2. Use twice daily, (morning and evening) or as recommended by a dentist or physician. Make sure to brush all sensitive areas of the teeth. Children under 12 years of age: consult a dentist or physician.

How Supplied

3.4 FL OZ (100mL) net wt. tube | NDC 69367-318-01 Mild Mint

STORAGE

Store at Controlled Room Temperature, 20°-25°C (68°-77°F)

REFERENCES

1. American Dental Association, Accepted Dental Therapeutics, Ed. 40, Chicago, ADA, 405-407(1984).
2. H.R. Englander et al., JADA, 75, 638-644 (1967).
3. H.R. Englander et al., JADA, 78, 783-787 (1969).
4. H.R. Englander et al., JADA, 82, 354-358 (1971).

Manufactured for:
Westminster Pharmaceuticals, LLC
Nashville, TN 37217
Rev. 02/24

PRINCIPAL DISPLAY PANEL - 100 mL Tube Carton

MILD MINT

NDC 69367-318-01
Rx Only

Sodium Fluoride 1.1% and Potassium Nitrate 5%

Prescription Strength Toothpaste for Sensitive Teeth

Sensitive

3.4 FL OZ (100 mL)

Westminster
Pharmaceuticals